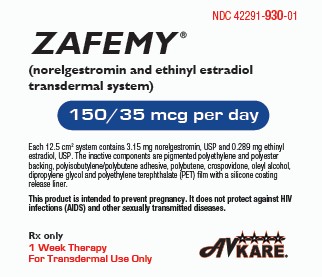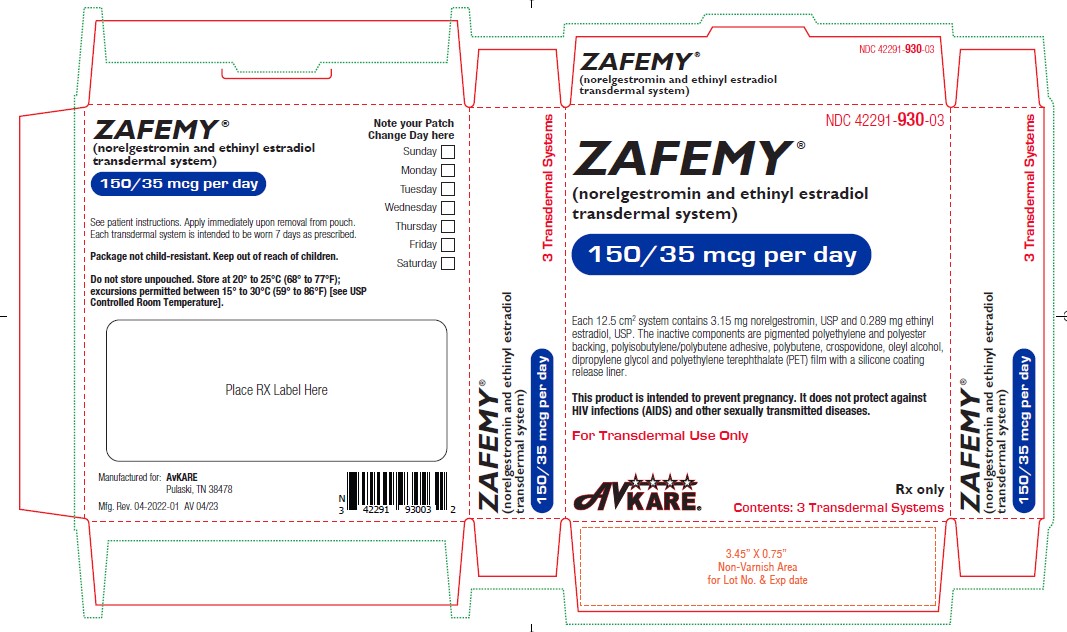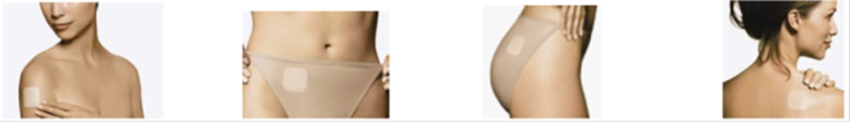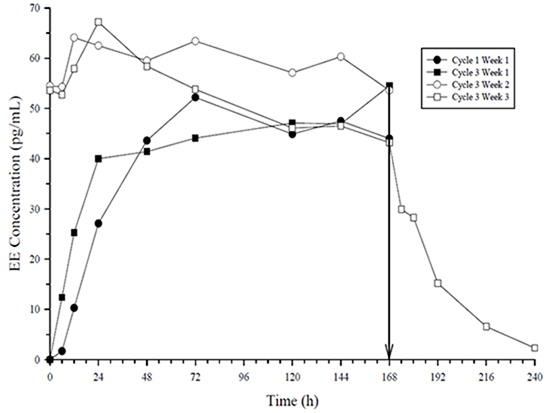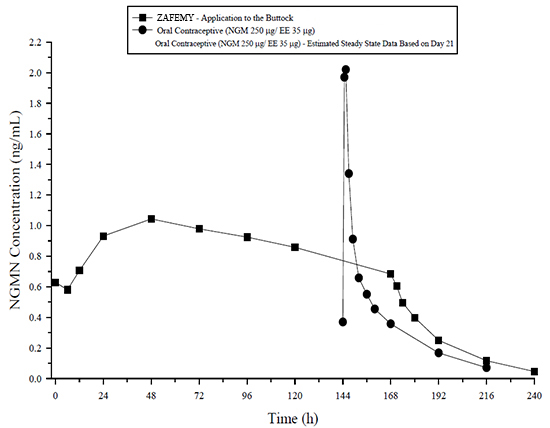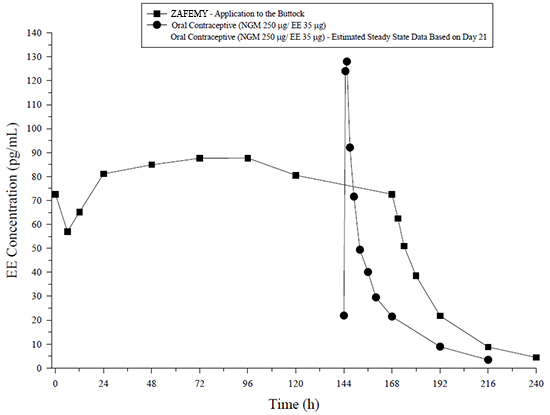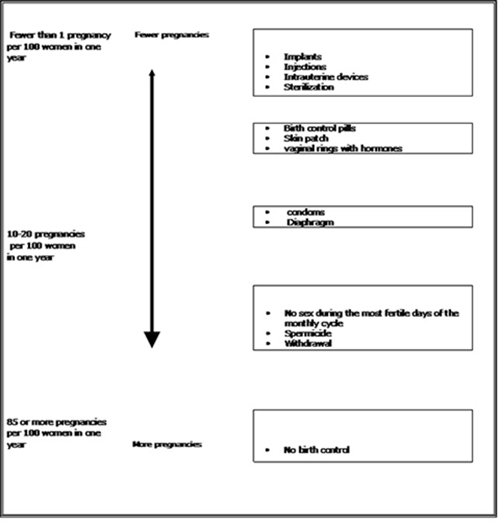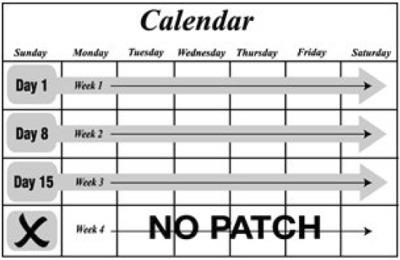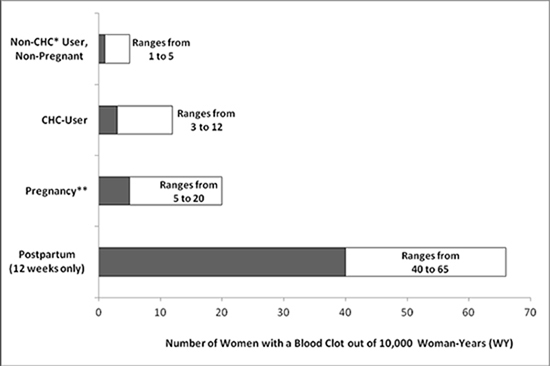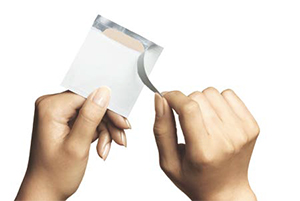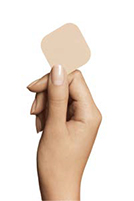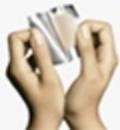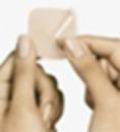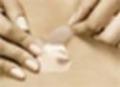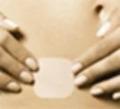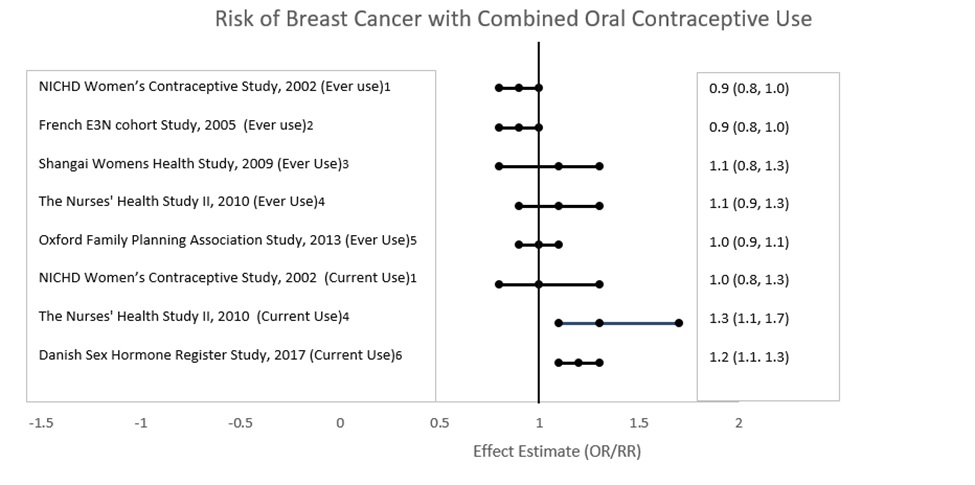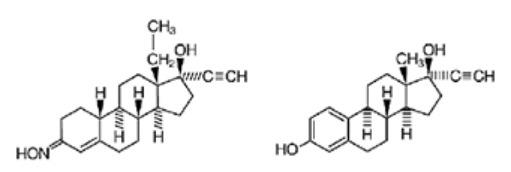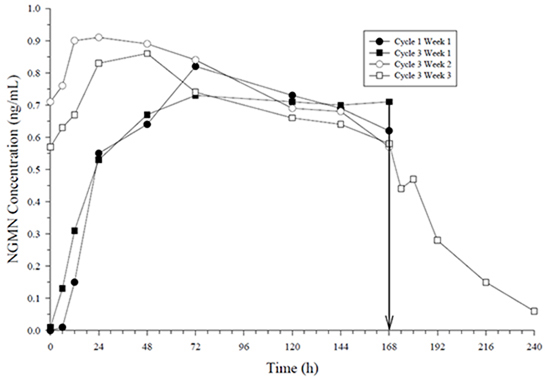 DRUG LABEL: ZAFEMY
NDC: 42291-930 | Form: PATCH
Manufacturer: AvKARE
Category: prescription | Type: HUMAN PRESCRIPTION DRUG LABEL
Date: 20260119

ACTIVE INGREDIENTS: NORELGESTROMIN 150 ug/1 d; ETHINYL ESTRADIOL 35 ug/1 d
INACTIVE INGREDIENTS: POLYBUTENE (1400 MW); CROSPOVIDONE; OLEYL ALCOHOL; DIPROPYLENE GLYCOL

HIGHLIGHTS OF PRESCRIBING INFORMATION

ZAFEMY ® (norelgestromin and ethinyl estradiol transdermal system)
These highlights do not include all the information needed to use ZAFEMY safely and effectively. See full prescribing information for ZAFEMY.
ZAFEMY® (norelgestromin and ethinyl estradiol transdermal system)
Initial U.S. Approval: 2001

WARNING: CIGARETTE SMOKING AND SERIOUS CARDIOVASCULAR EVENTS and CONTRAINDICATED IN WOMEN WITH A BMI ≥ 30 kg/m2

WARNING: CIGARETTE SMOKING AND SERIOUS CARDIOVASCULAR EVENTS and CONTRAINDICATED IN WOMEN WITH A BMI ≥ 30 kg/m^2

See full prescribing information for complete boxed warning.

- ZAFEMY is contraindicated in women over 35 years old who smoke. Cigarette smoking increases the risk of serious cardiovascular events from combination hormonal contraceptive (CHC) use. (4, 5.1)

- ZAFEMY is contraindicated for use in women with a BMI ≥ 30 kg/m^2. Women with a BMI ≥ 30 kg/m^2 who use ZAFEMY may have a higher risk of venous thromboembolic events compared with women with a lower BMI. (4, 5.1, 8.8)

RECENT MAJOR CHANGES

Warnings and Precautions (5.12) 11/2021

1 INDICATIONS AND USAGE

ZAFEMY® is an estrogen/progestin combination hormonal contraceptive (CHC), indicated for the prevention of pregnancy in women with a BMI < 30 kg/m^2 for whom a combined hormonal contraceptive is appropriate. (1)

Limitations of Use: ZAFEMY may be less effective in preventing pregnancy in women at or above 198 lbs (90 kg). (1, 4, 14)

2 DOSAGE AND ADMINISTRATION

- ZAFEMY uses a 28-day (four-week) cycle. Apply a new patch to the upper outer arm, abdomen, buttock or back each week for three weeks (21 total days). Week Four is patch-free. (2.1,2.3)
- Apply each new patch on the same day of the week. Wear only one patch at a time. (2.1)
- Do not cut or alter the patch in any way. (2.1)

3 DOSAGE FORMS AND STRENGTHS

Transdermal system: 150 mcg/day norelgestromin, USP and 35 mcg/day ethinyl estradiol, USP. (3)

4 CONTRAINDICATIONS

- At high risk of arterial or venous thromboembolic events (4)
- BMI ≥ 30 kg/m^2 (4)
- Breast cancer or other estrogen- or progestin-sensitive cancer (4)
- Liver tumors or liver disease (4)
- Undiagnosed abnormal uterine bleeding (4)
- Pregnancy (4)
- Co-administration with Hepatitis C drug combinations containing ombitasvir/paritaprevir/ritonavir, with or without dasabuvir (4)

5 WARNINGS AND PRECAUTIONS

- Vascular risks: Stop ZAFEMY if a thrombotic event occurs. Stop at least 4 weeks before and through 2 weeks after major surgery. Start no earlier than 4 weeks after delivery, in women who are not breastfeeding. Consider cardiovascular risk factors before initiating in all women, particularly those over 35 years. (5.1)
- Liver disease: Discontinue ZAFEMY if jaundice occurs. (5.3)
- High blood pressure: Do not prescribe ZAFEMY for women with uncontrolled hypertension or hypertension with vascular disease. (5.5)
- Carbohydrate and lipid metabolic effects: Monitor prediabetic and diabetic women taking ZAFEMY. Consider an alternate contraceptive method for women with uncontrolled dyslipidemia. (5.7)
- Headache: Evaluate significant change in headaches and discontinue ZAFEMY if indicated. (5.8)
- Uterine bleeding: Evaluate irregular bleeding or amenorrhea. (5.9)

6 ADVERSE REACTIONS

The most frequent adverse reactions reported during clinical trials (≥ 5%) were breast symptoms, nausea/vomiting, headache, application site disorder, abdominal pain, dysmenorrhea, vaginal bleeding and menstrual disorders, and mood, affect and anxiety disorders. (6.1)

To report SUSPECTED ADVERSE REACTIONS, contact AvKARE at 1-855-361-3993 or FDA at 1-800-FDA-1088 or www.fda.gov/medwatch.

7 DRUG INTERACTIONS

Drugs or herbal products that induce certain enzymes (for example CYP3A4) may decrease the effectiveness of CHCs or increase breakthrough bleeding. Counsel patients to use a back-up or alternative method of contraception when enzyme inducers are used with CHCs. (7.1)

8 USE IN SPECIFIC POPULATIONS

- Nursing mothers: Not recommended; can decrease milk production. (8.3)

FULL PRESCRIBING INFORMATION

WARNING: CIGARETTE SMOKING AND SERIOUS CARDIOVASCULAR EVENTS and CONTRAINDICATED IN WOMEN WITH A BMI ≥ 30 kg/m2

- Cigarette Smoking and Serious Cardiovascular Events
  Cigarette smoking increases the risk of serious cardiovascular events from hormonal contraceptive use. This risk increases with age, particularly in women over 35 years of age, and with the number of cigarettes smoked. For this reason, CHCs, including ZAFEMY, are contraindicated in women who are over 35 years of age and smoke [see Contraindications (4)and Warnings and Precautions (5.1)] .
- Contraindicated in Women with a BMI ≥ 30 kg/m^2

ZAFEMY is contraindicated in women with a BMI ≥ 30 kg/m^2. The risk of VTE may be greater with ZAFEMY in women with a BMI > 30 kg/m^2 compared to women with a lower BMI [see Contraindications (4)and Warnings and Precautions (5.1)] .

1 INDICATIONS AND USAGE

ZAFEMY® is indicated for the prevention of pregnancy in women with a body mass index (BMI) < 30 kg/m^2 for whom a combined hormonal contraceptive is appropriate.

Limitations of Use:

ZAFEMY may be less effective in preventing pregnancy in women who weigh 198 lbs (90 kg) or more. ZAFEMY is contraindicated for use in women with BMI ≥ 30 kg/m^2 [see Contraindications (4), Warnings and Precautions (5.1) and Clinical Studies (14)].

2 DOSAGE AND ADMINISTRATION

To achieve maximum contraceptive effectiveness, ZAFEMY must be used exactly as directed.

Complete instructions to facilitate patient counseling on proper system usage may be found in the FDA-Approved Patient Labeling.

2.1 How to Use ZAFEMY

The ZAFEMY transdermal system uses a 28-day (four-week) cycle. A new patch is applied each week for three weeks (21 total days). Week Four is patch-free. Withdrawal bleeding is expected during this time.

Every new patch should be applied on the same day of the week. This day is known as the “Patch Change Day.” For example, if the first patch is applied on a Monday, all subsequent patches should be applied on a Monday. Only one patch should be worn at a time.

Do not cut, damage or alter the ZAFEMY patch in any way. If the ZAFEMY patch is cut, damaged or altered in size, contraceptive efficacy may be impaired.

On the day after Week Four ends, a new four-week cycle is started by applying a new patch. Under no circumstances should there be more than a seven-day patch-free interval between dosing cycles.

2.2 How to Start Using ZAFEMY

There are multiple options for starting the ZAFEMY patch, and the woman should choose the option that is most appropriate (see Table 1):

Table 1: Instructions for Administration

Starting ZAFEMY patch in women with no current use of hormonal contraception
The woman has two options for starting the patch and she should choose the option that is right for her:
First Day Start
- The woman should apply her first patch during the first 24 hours of her menstrual period. If a patch is applied after the first 24 hours of menstruation, non-hormonal back-up contraception (such as condoms and spermicide, or diaphragm and spermicide) is needed for the first 7 days of the first cycle only.
- The woman should apply a new patch each week for three weeks (21 total days). Every new patch should be applied on the same day of the week. This day is known as the “Patch Change Day.” For example, if the first patch is applied on a Monday, all subsequent patches should be applied on a Monday. Only one patch should be worn at a time.
- No patch is worn during Week Four (the “Patch-Free Week”). Withdrawal bleeding is expected during this time.
- On the day after Week 4 ends, a new 4-week cycle is started by applying a new patch. Under no circumstances should there be more than a 7-day patch-free interval between dosing cycles.
Sunday Start
- The woman should apply her first patch on the first Sunday after her menstrual period begins.
- With this option, a non-hormonal backup method of birth control, such as a condom and spermicide or diaphragm and spermicide, is needed for the first 7 days of the first cycle only.
- If her period starts on a Sunday, the first patch should be applied that day, and no backup contraception is needed.
Switching from another contraceptive method
Oral combination hormonal contraception (oral CHC) | - If the woman is switching from the pill to ZAFEMY patch, she should complete her current pill cycle and apply the first ZAFEMY patch on the day she would normally start her next pill - If she does not get her period within a week after taking the last active pill, she should check with her healthcare professional to be sure that she is not pregnant, but she may go ahead and start ZAFEMY patch for contraception. - If the patch is applied more than a week after taking the last active pill, she should use a non-hormonal back-up contraception (such as condoms and spermicide, or diaphragm and spermicide) concurrently for the first 7 days of patch use.
Transdermal system | - If the woman is switching from another contraceptive transdermal system to ZAFEMY patch, she should complete the current transdermal system cycle and apply the first ZAFEMY patch on the day the next transdermal system cycle would normally start. - If she does not get her period within a week after removing the last transdermal system, she should check with her healthcare professional to be sure that she is not pregnant, but she may go ahead and start ZAFEMY patch for contraception. If ZAFEMY patch is applied more than a week after removal of the last patch, non-hormonal back-up contraception (such as condoms and spermicide, or diaphragm and spermicide) should be used concurrently for the first 7 days of patch use.
Vaginal ring | - If the woman is switching from the vaginal ring to ZAFEMY patch, she should complete her current vaginal ring cycle and apply the first ZAFEMY patch on the day she would normally insert her next vaginal ring. - If she does not get her period within a week after removing the last vaginal ring, she should check with her healthcare professional to be sure that she is not pregnant, but she may go ahead and start ZAFEMY patch for contraception. - If the patch is applied more than a week after removal of the last vaginal ring, she should use a non-hormonal back-up contraception (such as condoms and spermicide, or diaphragm and spermicide) concurrently for the first 7 days of patch use.
Injection | - If the woman is switching from an injection contraceptive to ZAFEMY patch, she should apply the first ZAFEMY patch on the day the next injection would normally occur.
Intrauterine system (IUS) | - If the woman is switching from an intrauterine system to ZAFEMY patch, she should apply the first ZAFEMY patch on the day of IUS removal. If the IUS is not removed on the first day of the menstrual cycle, non-hormonal backup contraception (such as condoms and spermicide, or diaphragm and spermicide) should be used concurrently for the first 7 days of patch use.
Implant | - If the woman is switching from an implant to ZAFEMY patch, she should apply the first ZAFEMY patch on the day of implant removal.
Progestin-only pill | - If the woman is switching from a progestin-only pill to ZAFEMY patch, she should apply the first ZAFEMY patch on the day the next progestin-only pill cycle would normally start.

Use after Childbirth

Start contraceptive therapy with ZAFEMY in women who elect not to breastfeed no sooner than 4 weeks after childbirth due to increased risk of thromboembolism. If a woman begins using ZAFEMY postpartum, and has not yet had a period, consider the possibility of ovulation and conception occurring prior to use of ZAFEMY, and instruct her to use an additional method of contraception, such as a condom and spermicide or diaphragm and spermicide, for the first seven days [see Warnings and Precautions (5.1)and Pregnancy (8.1)] .

Use after Abortion or Miscarriage

After an abortion or miscarriage that occurs in the first trimester, ZAFEMY may be started immediately. An additional method of contraception is not needed if ZAFEMY is started immediately. If use of ZAFEMY is not started within 5 days following a first trimester abortion, the woman should follow the instructions for a woman starting ZAFEMY for the first time. In the meantime she should be advised to use a non-hormonal contraceptive method. Ovulation may occur within 10 days of an abortion or miscarriage.

Start ZAFEMY no earlier than 4 weeks after a second trimester abortion or miscarriage, due to the increased risk of thromboembolic disease [see Contraindications (4)and Warnings and Precautions (5.1)] .

2.3 How to Apply ZAFEMY

CHOOSING A PLACE ON THE BODY TO PUT THE PATCH

- The patch may be placed on the upper outer arm, abdomen, buttock or back in a place where it won’t be rubbed by tight clothing. For example, it should not be placed under the waistband of clothing.
- The patch should not be placed on the breasts, on cut or irritated skin, or on the same location as the previous patch.

Before applying the patch:

- The woman should make sure the skin is clean and dry.
- She should not use lotions, creams, oils, powders, or make-up at the patch site. It may cause the patch to fail to stick properly or to become loose.

HOW TO APPLY THE PATCH

- The woman should tear open the pouch at the top edge. She should peel open the foil pouch that contains the patch and its clear plastic cover. She should gently remove the patch and its plastic cover together from the pouch, being careful not to separate the patch from the clear plastic cover.

- Using a fingernail, the woman should peel away half of the clear plastic. She should avoid touching the sticky surface with her fingers.

- The woman should apply the sticky side of the patch on the skin she has cleaned and dried. She should then remove the other half of the clear plastic and attach the entire patch to her skin.

- The woman should press firmly on the patch with the palm of her hand for 10 seconds, making sure that the whole patch adheres to her skin.
- She should run her fingers over the entire surface area to smooth out any “wrinkles” around the outer edges of the patch.

- The woman should check her patch every day to make sure all edges are sticking correctly.

WHEN TO CHANGE THE ZAFEMY PATCH

- The patch works for seven days (one week). The woman should apply a new patch on the same day each week (her Patch Change Day) for 3 weeks in a row. She must make sure she has removed her old patch prior to applying the new patch.
- During Week 4, she DOES NOT wear a patch. She must make sure she removes her old patch. (Her period should begin during this week.)
- Following Week 4, she repeats the cycle of three weekly applications followed by a patch-free week.

WHAT IF THE PATCH BECOMES LOOSE OR FALLS OFF?

The patch must stick securely to the skin to work properly. If the ZAFEMY patch becomes partially or completely detached and remains detached, insufficient drug delivery occurs. The woman should not try to reapply a patch if it is no longer sticky, if it has become stuck to itself or another surface, or if it has other material stuck to it.

If a patch edge lifts up:

- The woman should press down firmly on the patch with the palm of her hand for 10 seconds, making sure that the whole patch adheres to her skin. She should run her fingers over the entire surface area to smooth out any “wrinkles” around the edges of the patch.
- If her patch does not stick completely, she should remove it and apply a replacement patch.
- She should not tape or wrap the patch to her skin or reapply a patch that is partially adhered to clothing.

If the patch has been off or partially off:

- For less than 1 Day, she should try to reapply it. If the patch does not adhere completely, she should apply a new patch immediately. (No backup contraception is needed and her Patch Change Day will stay the same).
- For more than 1 Day or if she is not sure for how long, she may not be protected from pregnancy. To reduce this risk, she should apply a new patch and start a new 4-week cycle. She will now have a new Patch Change Day and MUST USE NON-HORMONAL BACKUP CONTRACEPTION (such as a condom and spermicide or diaphragm and spermicide) for the first week of her new cycle.

IF THE WOMAN FORGETS TO CHANGE HER PATCH

- at the start of any patch cycle (Week One/Day 1): SHE MAY NOT BE PROTECTED FROM PREGNANCY. She should apply the first patch of her new cycle as soon as she remembers. There is now a new “Patch Change Day” and a new “Day 1.” The woman must use back-up contraception, such as a condom and spermicide or diaphragm and spermicide, for the first week of the new cycle.
- in the middle of the patch cycle (Week Two/Day 8 or Week Three/Day 15),
  - for one or two days (up to 48 hours), she should apply a new patch immediately. The next patch should be applied on the usual “Patch Change Day.” No back-up contraception is needed.
  - for more than two days (48 hours or more), SHE MAY NOT BE PROTECTED FROM PREGNANCY. She should stop the current contraceptive cycle and start a new four-week cycle immediately by putting on a new patch. There is now a new “Patch Change Day” and a new “Day 1.” The woman must use back-up contraception for one week.
- at the end of the patch cycle (Week Four/Day 22),
  - If the woman forgets to remove her patch, she should take it off as soon as she remembers. The next cycle should be started on the usual “Patch Change Day,” which is the day after Day 28. No back-up contraception is needed.

Under no circumstances should there be more than a seven-day patch-free interval between cycles. If there are more than seven patch-free days, THE WOMAN MAY NOT BE PROTECTED FROM PREGNANCY and back-up contraception, such as a condom and spermicide or diaphragm and spermicide, must be used for seven days. As with combined oral contraceptives, the risk of ovulation increases with each day beyond the recommended drug-free period. If she has had intercourse during such an extended patch-free interval, consider the possibility of pregnancy.

Change Day Adjustment

If the woman wishes to change her Patch Change Day, she should complete her current cycle, removing the third ZAFEMY patch on the correct day. During the patch-free week, she may select an earlier Patch Day Change by applying a new ZAFEMY patch on the desired day. In no case should there be more than 7 consecutive patch-free days.

Breakthrough Bleeding or Spotting

In the event of unscheduled or breakthrough bleeding or spotting (bleeding that occurs on the days that ZAFEMY is worn), treatment should be continued. If unscheduled bleeding persists longer than a few cycles, consider causes other than ZAFEMY.

If the woman does not have scheduled or withdrawal bleeding (bleeding that should occur during the patch-free week), she should resume treatment on the next scheduled Change Day. If ZAFEMY has been used correctly, the absence of withdrawal bleeding is not necessarily an indication of pregnancy. Nevertheless, consider the possibility of pregnancy, especially if absence of withdrawal bleeding occurs in 2 consecutive cycles. Discontinue ZAFEMY if pregnancy is confirmed.

In Case of Skin Irritation

If patch use results in uncomfortable irritation, the patch may be removed and a new patch may be applied to a different location until the next Change Day. Only one patch should be worn at a time.

Additional Instructions for Dosing

Unscheduled bleeding, spotting, and amenorrhea are frequent reasons for patients discontinuing hormonal contraceptives. In case of breakthrough bleeding, as in all cases of irregular bleeding from the vagina, consider nonfunctional causes. In case of undiagnosed persistent or recurrent abnormal bleeding from the vagina, take adequate diagnostic measures to rule out pregnancy or malignancy. If pathology has been excluded, time or a change to another method of contraception may solve the problem.

Use of Hormonal Contraceptives in the Event of a Missed Menstrual Period

1. If the woman has not adhered to the prescribed schedule, consider the possibility of pregnancy at the time of the first missed period. Discontinue use of ZAFEMY if pregnancy is confirmed.
2. If the woman has adhered to the prescribed regimen and misses one period, she should continue using her contraceptive patches. However, if she has adhered to the prescribed regimen, misses one period and has symptoms associated with pregnancy, rule out pregnancy. Discontinue ZAFEMY use if pregnancy is confirmed.
3. If the woman has adhered to the prescribed regimen and misses two consecutive periods, rule out pregnancy. Discontinue ZAFEMY use if pregnancy is confirmed.

3 DOSAGE FORMS AND STRENGTHS

Transdermal system: 150 mcg/day norelgestromin, USP and 35 mcg/day ethinyl estradiol, USP.

4 CONTRAINDICATIONS

ZAFEMY is contraindicated in females who are known to have or develop the following conditions:

- At high risk of arterial or venous thromboembolic events. Examples include women who:

- Smoke, if over age 35 [see Boxed Warning, and Warnings and Precautions (5.1)]
- Have deep vein thrombosis or pulmonary embolism, now or in the past [see Warnings and Precautions (5.1)]
- Have inherited or acquired hypercoagulopathies [see Warnings and Precautions (5.1)]
- Have cerebrovascular disease [see Warnings and Precautions (5.1)]
- Have coronary artery disease [see Warnings and Precautions (5.1)]
- Have thrombogenic valvular or thrombogenic rhythm diseases of the heart (for example, subacute bacterial endocarditis with valvular disease, or atrial fibrillation) [see Warnings and Precautions (5.1)]
- Have uncontrolled hypertension [see Warnings and Precautions (5.5)]
- Have diabetes mellitus with vascular disease [see Warnings and Precautions (5.7)]
- Have headaches with focal neurological symptoms or have migraine headaches with aura

- Women over age 35 with any migraine headaches [see Warnings and Precautions (5.8)]

- Body Mass Index ≥ 30 kg/m^2 [see Warnings and Precautions (5.1)]
- Liver tumors, benign or malignant, or liver disease [see Warnings and Precautions (5.3), Use in Specific Populations (8.6)and Clinical Pharmacology (12.3)]
- Undiagnosed abnormal uterine bleeding [see Warnings and Precautions (5.9)]
- Pregnancy, because there is no reason to use hormonal contraceptives during pregnancy [see Warnings and Precautions (5.10)and Use in Specific Populations (8.1)]
- Current diagnosis of, or history of, breast cancer, which may be hormone-sensitive [see Warnings and Precautions (5.12)]
- Use of Hepatitis C drug combinations containing ombitasvir/paritaprevir/ritonavir, with or without dasabuvir, due to the potential for ALT elevations [see Warnings and Precautions (5.4)]

5 WARNINGS AND PRECAUTIONS

5.1 Thromboembolic Disorders and Other Vascular Conditions

- Stop ZAFEMY if an arterial or venous thromboembolic event (VTE) occurs.
- Stop ZAFEMY if there is unexplained loss of vision, proptosis, diplopia, papilledema, or retinal vascular lesions. Evaluate for retinal vein thrombosis immediately.
- If feasible, stop ZAFEMY at least 4 weeks before and through 2 weeks after major surgery or other surgeries known to have an elevated risk of VTE. Discontinue use of ZAFEMY during prolonged immobilization and resume treatment based on clinical judgment.
- Start ZAFEMY no earlier than 4 weeks after delivery, in women who are not breastfeeding. The risk of postpartum VTE decreases after the third postpartum week, whereas the risk of ovulation increases after the third postpartum week.
- Before starting ZAFEMY, evaluate any past medical history or family history of thrombotic or thromboembolic disorders and consider whether the history suggests an inherited or acquired hypercoagulopathy [see Contraindications (4)] .

Arterial Events

The use of CHCs increases the risk of cardiovascular events and cerebrovascular events, such as myocardial infarction and stroke. The risk is greater among older women (> 35 years of age), smokers, and women with hypertension, dyslipidemia, diabetes, or obesity. ZAFEMY is contraindicated in women over 35 years of age who smoke [see Contraindications (4)] . Cigarette smoking increases the risk of serious cardiovascular events from CHC use. This risk increases with age, particularly in women over 35 years of age, and with the number of cigarettes smoked.

Venous Events

The use of CHCs increases the risk of venous thromboembolic events (VTEs), such as deep vein thrombosis and pulmonary embolism. Risk factors for VTEs include smoking, obesity, and family history of VTE, in addition to other factors that contraindicate use of CHCs. The risk of VTE may be greater with ZAFEMY in women with a BMI ≥ 30 kg/m^2 compared to women with a lower BMI [see Contraindications (4)] .

While the risk of VTE associated with the use of CHCs is well-established, the rates of VTE are even greater during pregnancy, and especially during the post-partum period (see Figure 1). The frequency of VTE in women using CHCs has been estimated to be 3 to 12 cases per 10,000 woman-years.

The risk of VTE is highest during the first year of use of CHCs and when restarting hormonal contraception after a break of 4 weeks or longer. This initial higher risk declines during the first year, but users of CHCs remain at an increased risk of VTE compared to non-users of CHCs. Based on results from a few studies, there is some evidence that this is true for non-oral products as well. The risk of thromboembolic disease due to CHCs gradually disappears after CHC use is discontinued.

Figure 1 shows the risk of developing a VTE for women who are not pregnant and do not use CHCs, for women who use CHCs with a range of doses and routes of administration, for pregnant women, and for women in the post-partum period. To put the risk of developing a VTE into perspective: If 10,000 women who are not pregnant and do not use CHCs are followed for one year, between 1 and 5 of these women will develop a VTE.

Figure 1: Likelihood of Developing a VTE Within One Year Among Pregnant and Non-Pregnant Women

*CHC = combination hormonal contraception

**Pregnancy data based on actual duration of pregnancy in the reference studies. Based on a model assumption that pregnancy duration is nine months, the rate is 7 to 27 per 10,000 WY.

5.2 Ethinyl Estradiol Exposure

Higher estrogen exposure may increase the risk of adverse reactions, including venous thromboembolism (VTE). The Area Under the Curve (AUC) for ethinyl estradiol (EE) is approximately 60% higher in women using ZAFEMY compared to oral contraceptives containing EE 35 mcg. In contrast, the peak concentration (Cmax) for EE is approximately 25% lower in women using ZAFEMY [see Clinical Pharmacology (12.3)] .

5.3 Liver Disease

Impaired Liver Function

Do not use ZAFEMY in women with liver disease, such as acute viral hepatitis or severe (decompensated) cirrhosis of liver [see Contraindications (4)] . Discontinue ZAFEMY if jaundice develops. Acute or chronic disturbances of liver function may necessitate the discontinuation of CHC use until markers of liver function return to normal and CHC causation has been excluded.

Liver Tumors

ZAFEMY is contraindicated in women with benign and malignant liver tumors [see Contraindications (4)] . Hepatic adenomas are associated with CHC use. An estimate of the attributable risk is 3.3 cases/100,000 CHC users. Rupture of hepatic adenomas may cause death through intra-abdominal hemorrhage.

Studies have shown an increased risk of developing hepatocellular carcinoma in long-term (>8 years) CHC users. However, the risk of liver cancers in CHC users is less than one case per million users.

5.4 Risk of Liver Enzyme Elevations with Concomitant Hepatitis C Treatment

During clinical trials with the Hepatitis C combination drug regimen that contains ombitasvir/paritaprevir/ritonavir, with or without dasabuvir, ALT elevations greater than 5 times the upper limit of normal (ULN), including some cases greater than 20 times the ULN, were significantly more frequent in women using ethinyl estradiol-containing medications, such as CHCs. Discontinue ZAFEMY prior to starting therapy with the combination drug regimen ombitasvir/paritaprevir/ritonavir, with or without dasabuvir [see Contraindications (4)] . ZAFEMY can be restarted approximately 2 weeks following completion of treatment with the Hepatitis C combination drug regimen.

5.5 High Blood Pressure

ZAFEMY is contraindicated in women with uncontrolled hypertension or hypertension with vascular disease [see Contraindications (4)] . For women with well-controlled hypertension, monitor blood pressure and stop ZAFEMY if blood pressure rises significantly.

An increase in blood pressure has been reported in women taking hormonal contraceptives, and this increase is more likely in older women with extended duration of use. The incidence of hypertension increases with increasing concentrations of progestin.

5.6 Gallbladder Disease

Studies suggest a small increased relative risk of developing gallbladder disease among CHC users. Use of CHCs may also worsen existing gallbladder disease. A past history of CHC-related cholestasis predicts an increased risk with subsequent CHC use. Women with a history of pregnancy-related cholestasis may be at an increased risk for CHC-related cholestasis.

5.7 Carbohydrate and Lipid Metabolic Effects

Carefully monitor prediabetic and diabetic women who take ZAFEMY. CHCs may decrease glucose tolerance in a dose-related fashion. In a 6-cycle clinical trial with ZAFEMY patch there were no clinically significant changes in fasting blood glucose from baseline to end of treatment.

Consider alternative contraception for women with uncontrolled dyslipidemia. A small proportion of women will have adverse lipid changes while on hormonal contraceptives.

Women with hypertriglyceridemia, or a family history thereof, may be at an increased risk of pancreatitis when using hormonal contraceptives.

5.8 Headache

If a woman taking ZAFEMY develops new headaches that are recurrent, persistent or severe, evaluate the cause and discontinue ZAFEMY if indicated.

Consider discontinuation of ZAFEMY in the case of increased frequency or severity of migraine during hormonal contraceptive use (which may be prodromal of a cerebrovascular event).

5.9 Bleeding Irregularities

Unscheduled Bleeding and Spotting

Unscheduled (breakthrough) bleeding and spotting sometimes occur in women using ZAFEMY. Consider non-hormonal causes and take adequate diagnostic measures to rule out malignancy, other pathology, or pregnancy in the event of unscheduled bleeding, as in the case of any abnormal vaginal bleeding. If pathology and pregnancy have been excluded, time or a change to another contraceptive product may resolve the bleeding.

In the clinical trials, most women started their scheduled (withdrawal) bleeding on the fourth day of the drug-free interval, and the median duration of withdrawal bleeding was 5 to 6 days. On average, 26% of women per cycle had 7 or more total days of bleeding and/or spotting (this includes both scheduled and unscheduled bleeding and/or spotting). Three clinical studies of the efficacy of ZAFEMY in preventing pregnancy assessed scheduled and unscheduled bleeding [see Clinical Studies (14)] in 3,330 women who completed 22,155 cycles of exposure. A total of 36 (1.1%) of the women discontinued ZAFEMY at least in part, due to bleeding or spotting.

Table 2 summarizes the proportion of subjects who experienced unscheduled (breakthrough) bleeding/spotting by treatment cycle.

Table 2: Unscheduled (Breakthrough) Bleeding/Spotting (Subjects Evaluable for Efficacy)
Treatment Cycle | Pooled data from 3 studies N=3,319
 | n | %a
Cycle 1 | 2,994 | 18.2
Cycle 2 | 2,743 | 11.9
Cycle 3 | 2,699 | 11.6
Cycle 4 | 2,541 | 10.1
Cycle 5 | 2,532 | 9.2
Cycle 6 | 2,494 | 8.3
Cycle 7 | 698 | 8.3
Cycle 8 | 692 | 8.7
Cycle 9 | 654 | 8.6
Cycle 10 | 621 | 8.7
Cycle 11 | 631 | 8.9
Cycle 12 | 617 | 6.3
Cycle 13 | 611 | 8.0
a Percentage of subjects with breakthrough bleeding/spotting events.

Amenorrhea and Oligomenorrhea

In the event of amenorrhea, consider the possibility of pregnancy. If the patient has not adhered to the prescribed dosing schedule (missed one patch or started the patch on a day later than she should have), consider the possibility of pregnancy at the time of the first missed period and take appropriate diagnostic measures. If the patient has adhered to the prescribed regimen and misses two consecutive periods, rule out pregnancy.

Some women may encounter amenorrhea or oligomenorrhea after discontinuation of hormonal contraceptive use, especially when such a condition was pre-existent.

5.10 Hormonal Contraceptive Use Before or During Early Pregnancy

Extensive epidemiological studies have revealed no increased risk of birth defects in women who have used oral contraceptives prior to pregnancy. Studies also do not suggest a teratogenic effect, particularly in so far as cardiac anomalies and limb reduction defects are concerned, when oral contraceptives are taken inadvertently during early pregnancy. Discontinue ZAFEMY use if pregnancy is confirmed.

Administration of CHCs should not be used as a test for pregnancy [see Use in Specific Populations (8.1)] .

5.11 Depression

Carefully observe women with a history of depression and discontinue ZAFEMY if depression recurs to a serious degree.

5.12 Malignant Neoplasms

Breast Cancer

ZAFEMY is contraindicated in females who currently have or have had breast cancer because breast cancer may be hormonally sensitive [see Contraindications (4)] . Epidemiology studies have not found a consistent association between use of combined oral contraceptives (COCs) and breast cancer risk. Studies do not show an association between ever (current or past) use of COCs and risk of breast cancer. However, some studies report a small increase in the risk of breast cancer among current or recent users (<6 months since last use) and current users with longer duration of COC use [see Postmarketing Experience (6.2)] .

Cervical Cancer

Some studies suggest that combination oral contraceptive use has been associated with an increase in the risk of cervical cancer or intraepithelial neoplasia. However, there continues to be controversy about the extent to which such findings may be due to differences in sexual behavior and other factors.

5.13 Effect on Binding Globulins

The estrogen component of CHCs may raise the serum concentrations of thyroxine-binding globulin, sex hormone-binding globulin and cortisol-binding globulin. The dose of replacement thyroid hormone or cortisol therapy may need to be increased.

5.14 Monitoring

A woman who is taking hormonal contraceptive should have routine visits with her healthcare provider for a blood pressure check and for other indicated healthcare.

5.15 Hereditary Angioedema

In women with hereditary angioedema, exogenous estrogens may induce or exacerbate symptoms of angioedema.

5.16 Chloasma

Chloasma may occasionally occur, especially in women with a history of chloasma gravidarum. Women with a tendency to chloasma should avoid exposure to the sun or ultraviolet radiation while using ZAFEMY.

6 ADVERSE REACTIONS

The following serious adverse reactions with the use of combination hormonal contraceptives, including ZAFEMY, are discussed elsewhere in the labeling:

- Serious cardiovascular events and stroke [see Boxed Warningand Warnings and Precautions (5.1)]
- Vascular events, including venous and arterial thromboembolic events [see Warnings and Precautions (5.1)]
- Liver disease [see Warnings and Precautions (5.3)]

Adverse reactions commonly reported by users of combination hormonal contraceptives are:

- Irregular uterine bleeding
- Nausea
- Breast tenderness
- Headache

6.1 Clinical Trials Experience

Because clinical trials are conducted under widely varying conditions, adverse reaction rates observed in the clinical trials of a drug cannot be directly compared to rates in the clinical trials of another drug and may not reflect the rates observed in clinical practice.

The data described below reflect exposure to ZAFEMY in 3,330 sexually active women (3,322 of whom had safety data) who participated in three Phase 3 clinical trials designed to evaluate contraceptive efficacy and safety. These subjects received six or 13 cycles of contraception (ZAFEMY or an oral contraceptive comparator in 2 of the trials). The women ranged in age from 18 to 45 years and were predominantly white (91%).

The most common adverse reactions (≥ 5%) reported during clinical trials were breast symptoms, nausea/vomiting, headache, application site disorder, abdominal pain, dysmenorrhea, vaginal bleeding and menstrual disorders, and mood, affect and anxiety disorders. The most common events leading to discontinuation were application site reaction, breast symptoms (including breast discomfort, engorgement and pain), nausea and/or vomiting, headache and emotional lability.

Adverse drug reactions reported by ≥ 2.5% of ZAFEMY-treated subjects in these trials are shown in Table 3.

Table 3: Adverse Drug Reactions Reported by ≥ 2.5% of ZAFEMY-treated Subjects in Three Phase 3 Clinical Trials
System/Organ Class* Adverse reaction | ZAFEMY (n=3,322)
Reproductive system and breast disorders
Breast symptoms† | 22.4%
Dysmenorrhea | 7.8%
Vaginal bleeding and menstrual disorders† | 6.4%
Gastrointestinal disorders
Nausea | 16.6%
Abdominal pain† | 8.1%
Vomiting | 5.1%
Diarrhea | 4.2%
Nervous system disorders
Headache | 21.0%
Dizziness | 3.3%
Migraine | 2.7%
General disorders and administration site conditions
Application site disorder† | 17.1%
Fatigue | 2.6%
Psychiatric disorders
Mood, affect and anxiety disorders† | 6.3%
Skin and subcutaneous tissue disorders
Acne | 2.9%
Pruritus | 2.5%
Infections and infestations
Vaginal yeast infection† | 3.9%
Investigations
Weight increased | 2.7%
* MedDRA version 10.0
† Represents a bundle of similar terms

Additional adverse drug reactions that occurred in < 2.5% of ZAFEMY-treated subjects in the above clinical trials datasets are:

- Gastrointestinal disorders: Abdominal distension
- General disorders and administration site conditions: Fluid retention^1, malaise
- Hepatobiliary disorders: Cholecystitis
- Investigations: Blood pressure increased, lipid disorders^1
- Musculoskeletal and connective tissue disorders: Muscle spasms
- Psychiatric disorders: Insomnia, libido decreased, libido increased
- Reproductive system and breast disorders: Galactorrhea, genital discharge, premenstrual syndrome, uterine spasm, vaginal discharge, vulvovaginal dryness
- Respiratory, thoracic and mediastinal disorders: Pulmonary embolism
- Skin and subcutaneous tissue disorders: Chloasma, dermatitis contact, erythema, skin irritation

^1Represents a bundle of similar terms

6.2 Postmarketing Experience

Five studies that compared breast cancer risk between ever-users (current or past use) of COCs and never-users of COCs reported no association between ever use of COCs and breast cancer risk, with effect estimates ranging from 0.90 to 1.12 (Figure 2).

Three studies compared breast cancer risk between current or recent COC users (<6 months since last use) and never users of COCs (Figure 2). One of these studies reported no association between breast cancer risk and COC use. The other two studies found an increased relative risk of 1.19 to 1.33 with current or recent use. Both of these studies found an increased risk of breast cancer with current use of longer duration, with relative risks ranging from 1.03 with less than one year of COC use to approximately 1.4 with more than 8 to 10 years of COC use.

Figure 2:

RR = relative risk; OR = odds ratio; HR = hazard ratio. “ever COC” are females with current or past COC use; “never COC use” are females that never used COCs.
The following adverse reactions (Table 4) have been identified during post-approval use of ZAFEMY. Because these reactions are reported voluntarily from a population of uncertain size, it is not always possible to reliably estimate their frequency or establish a causal relationship to drug exposure.

Table 4: Alphabetical List of Adverse Drug Reactions Identified During Postmarketing Experience with ZAFEMY by System Organ Class*
System Organ Class | Adverse Drug Reactions
Cardiac disorders | Myocardial infarction†
Endocrine disorders | Hyperglycemia, insulin resistance
Eye disorders | Contact lens intolerance or complication
Gastrointestinal disorders | Colitis
General disorders and administration site conditions | Application site reaction†, edema†
Hepatobiliary disorders | Blood cholesterol abnormal, cholelithiasis, cholestasis, hepatic lesion, jaundice cholestatic, low density lipoprotein increased
Immune system disorders | Allergic reaction†, urticaria
Investigations | Blood glucose abnormal, blood glucose decreased
Metabolism and nutrition disorders | Increased appetite
Neoplasms benign, malignant and unspecified (Incl. cysts and polyps) | Breast cancer†, cervix carcinoma, hepatic adenoma, hepatic neoplasm
Nervous system disorders | Dysgeusia, migraine with aura
Psychiatric disorders | Anger, emotional disorder, frustration, irritability
Reproductive system and breast disorders | Breast mass, cervical dysplasia, fibroadenoma of breast, menstrual disorder†, suppressed lactation, uterine leiomyoma
Skin and subcutaneous tissues disorders | Alopecia, eczema, erythema multiforme, erythema nodosum, photosensitivity reaction, pruritus generalized, rash†, seborrheic dermatitis, skin reaction
Vascular disorders | Arterial thrombosis†, cerebrovascular accident†, deep vein thrombosis†, hemorrhage intracranial†, hypertension, hypertensive crisis, pulmonary embolism†, thrombosis†
* MedDRA version 10.0
† Represents a bundle of similar terms

7 DRUG INTERACTIONS

Consult the labeling of concurrently-used drugs to obtain further information about interactions with hormonal contraceptives or the potential for enzyme alterations.

7.1 Effects of Other Drugs on Combined Hormonal Contraceptives

Substances Decreasing the Plasma Concentrations of CHCs and Potentially Diminishing the Efficacy of CHCs:

Drugs or herbal products that induce certain enzymes, including cytochrome P450 3A4 (CYP3A4), may decrease the plasma concentrations of CHCs and potentially diminish the effectiveness of CHCs or increase breakthrough bleeding. Some drugs or herbal products that may decrease the effectiveness of hormonal contraceptives include phenytoin, barbiturates, carbamazepine, bosentan, felbamate, griseofulvin, oxcarbazepine, rifampicin, topiramate, rifabutin, rufinamide, aprepitant, and products containing St. John’s wort. Interactions between hormonal contraceptives and other drugs may lead to breakthrough bleeding and/or contraceptive failure. Counsel women to use an alternative method of contraception or a back-up method when enzyme inducers are used with CHCs, and to continue back-up contraception for 28 days after discontinuing the enzyme inducer to ensure contraceptive reliability.

Substances Increasing the Plasma Concentrations of CHCs:

Co-administration of atorvastatin or rosuvastatin and certain CHCs containing EE increase AUC values for EE by approximately 20% to 25%. Ascorbic acid and acetaminophen may increase plasma EE concentrations, possibly by inhibition of conjugation. CYP3A4 inhibitors such as itraconazole, voriconazole, fluconazole, grapefruit juice, or ketoconazole may increase plasma hormone concentrations.

Human Immunodeficiency Virus (HIV)/Hepatitis C Virus (HCV) Protease Inhibitors and Non-Nucleoside Reverse Transcriptase Inhibitors:

Significant changes (increase or decrease) in the plasma concentrations of estrogen and/or progestin have been noted in some cases of co-administration with HIV protease inhibitors (decrease [e.g., nelfinavir, ritonavir, darunavir/ritonavir, (fos)amprenavir/ritonavir, lopinavir/ritonavir, and tipranavir/ritonavir] or increase [e.g., indinavir and atazanavir/ritonavir])/HCV protease inhibitors or with non-nucleoside reverse transcriptase inhibitors (decrease [e.g., nevirapine] or increase [e.g., etravirine]).

7.2 Effects of Combined Hormonal Contraceptives on Other Drugs

CHCs containing EE may inhibit the metabolism of other compounds (e.g., cyclosporine, prednisolone, theophylline, tizanidine, and voriconazole) and increase their plasma concentrations. CHCs have been shown to decrease plasma concentrations of acetaminophen, clofibric acid, morphine, salicylic acid, and temazepam. Significant decrease in plasma concentration of lamotrigine has been shown, likely due to induction of lamotrigine glucuronidation. This may reduce seizure control; therefore, dosage adjustments of lamotrigine may be necessary.

Women on thyroid hormone replacement therapy may need increased doses of thyroid hormone because serum concentration of thyroid-binding globulin increases with use of CHCs [see Warnings and Precautions (5.13)] .

7.3 Concomitant Use with HCV Combination Therapy – Liver Enzyme Elevation

Do not co-administer ZAFEMY with HCV drug combinations containing ombitasvir/paritaprevir/ritonavir, with or without dasabuvir, due to potential for ALT elevations [see Warnings and Precautions (5.4)] .

7.4 Interference with Laboratory Tests

The use of contraceptive steroids may influence the results of certain laboratory tests, such as coagulation factors, lipids, glucose tolerance, and binding proteins.

8 USE IN SPECIFIC POPULATIONS

8.1 Pregnancy

There is little or no increased risk of birth defects in women who inadvertently use hormonal contraceptives during early pregnancy. Epidemiologic studies and meta-analyses have not found an increased risk of genital or non-genital birth defects (including cardiac anomalies and limb reduction defects) following exposure to low dose hormonal contraceptives prior to conception or during early pregnancy.

The administration of hormonal contraceptives to induce withdrawal bleeding should not be used as a test for pregnancy. Hormonal contraceptives should not be used during pregnancy to treat threatened or habitual abortion.

8.3 Nursing Mothers

The effects of ZAFEMY in nursing mothers have not been evaluated and are unknown. When possible, advise the nursing mother to use other forms of contraception until she has completely weaned her child. Estrogen-containing CHCs can reduce milk production in breastfeeding mothers. This is less likely to occur once breastfeeding is well-established; however, it can occur at any time in some women. Small amounts of contraceptive steroids and/or metabolites are present in breast milk.

8.4 Pediatric Use

Safety and efficacy of ZAFEMY have been established in women of reproductive age. Efficacy is expected to be the same for post-pubertal adolescents under the age of 18 and for users 18 years and older. Use of this product before menarche is not indicated.

8.5 Geriatric Use

ZAFEMY has not been studied in postmenopausal women and is not indicated in this population.

8.6 Hepatic Impairment

No studies with ZAFEMY have been conducted in women with hepatic impairment. However, steroid hormones may be poorly metabolized in patients with impaired liver function. Acute or chronic disturbances of liver function may necessitate the discontinuation of combined hormonal contraceptive use until markers of liver function return to normal and combined hormonal contraceptive causation has been excluded [see Contraindications (4)and Warnings and Precautions (5.3)] .

8.7 Renal Impairment

No studies with ZAFEMY have been conducted in women with renal impairment.

8.8 BMI and Weight Considerations

ZAFEMY is contraindicated in women with a BMI ≥ 30 kg/m^2 because of the potential increased risk of VTE [see Contraindications (4)and Warnings and Precautions (5.1)] .

ZAFEMY may be less effective in preventing pregnancy in women who weigh 198 lbs or more [see Clinical Studies (14)] .

10 OVERDOSAGE

Overdosage may cause nausea and vomiting, and withdrawal bleeding may occur in women. In case of suspected overdose, all ZAFEMY patches should be removed and symptomatic treatment given.

11 DESCRIPTION

ZAFEMY is a transdermal system with a contact surface area of 12.5 cm^2. It contains 3.15 mg norelgestromin, USP (NGMN) and 0.289 mg ethinyl estradiol, USP (EE), and its delivery rate is approximately 150 mcg of NGMN, USP and 35 mcg of EE, USP per day. Systemic exposures (as measured by area under the curve [AUC] and steady-state concentration [Css]) of NGMN, USP and EE, USP during use of ZAFEMY are higher and the Cmax is lower than those produced by an oral contraceptive containing norgestimate, USP (NGM) 250 mcg / EE, USP 35 mcg [see Boxed Warningand Clinical Pharmacology (12.3)] .

ZAFEMY is a thin, matrix-type transdermal system consisting of three layers. The backing layer is composed of a tan backing consisting of pigmented polyethylene and polyester. It provides structural support and protects the middle adhesive layer from the environment. The middle layer contains polyisobutylene/polybutene adhesive, polybutene, crospovidone, oleyl alcohol and dipropylene glycol as inactive components. The active components in this layer are the hormones, NGMN, USP and EE, USP. The third layer is the release liner, which protects the adhesive layer during storage and is removed just prior to application. It is a transparent polyethylene terephthalate (PET) film with a silicone coating on the side that is in contact with the middle adhesive layer.

The outside of the backing layer is printed with “Norelgestromin and Ethinyl Estradiol 150/35 mcg per day” in brown ink.

The structural formulas of the components are:

Norelgestromin, USP ethinyl estradiol, USP

Molecular weight, NGMN, USP: 327.47

Molecular weight, EE, USP: 296.41

Chemical name for NGMN, USP: 18, 19-Dinorpregn-4-en-20-yn-3-one, 13-ethyl-17-hydroxy-,3-oxime,(17α)

Chemical name for EE, USP: 19-Norpregna-1,3,5(10)-trien-20-yne-3, 17-diol,(17α)

12 CLINICAL PHARMACOLOGY

12.1 Mechanism of Action

NGMN is the active progestin largely responsible for the progestational activity that occurs in women following application of ZAFEMY. NGMN is also the primary active metabolite produced following oral administration of NGM, the progestin component of some oral contraceptive products.

Combination hormonal contraceptives act by suppression of gonadotropins. Although the primary mechanism of this action is inhibition of ovulation, other alterations include changes in the cervical mucus (which increase the difficulty of sperm entry into the uterus) and the endometrium (which reduce the likelihood of implantation).

12.2 Pharmacodynamics

One clinical trial assessed the return of hypothalamic-pituitary-ovarian axis function post-therapy and found that follicle-stimulating hormone (FSH), luteinizing hormone (LH), and estradiol mean values, though suppressed during therapy, returned to near baseline values during the 6 weeks post therapy.

12.3 Pharmacokinetics

Absorption

The systemic delivery rate of NGMN and EE from ZAFEMY is approximately 150 mcg of NGMN and 35 mcg of EE per day based on a comparative analysis with intravenous (IV) data. Following a single application of ZAFEMY, both NGMN and EE reach a plateau by approximately 48 hours. Pooled data from the 3 clinical studies have demonstrated that steady-state is reached within 2 weeks of application. In one of the clinical studies, Css concentrations across all subjects ranged from 0.305 to 1.53 ng/mL for NGMN and from 23 to 137 pg/mL for EE.

Absorption of NGMN and EE following application of ZAFEMY to the buttock, upper outer arm, abdomen and upper torso (excluding breast) was examined. While absorption from the abdomen was slightly lower than from other sites, absorption from these anatomic sites was considered to be therapeutically equivalent.

The mean (%CV) PK parameters Css and AUC0-168 for NGMN and EE following a single buttock application of ZAFEMY are summarized in Table 5.

In multiple dose studies, AUC0-168 for NGMN and EE was found to increase over time (Table 5). In a three-cycle study, these PK parameters reached steady-state conditions during Cycle 3 (Figures 5 and 4). Upon removal of the patch, serum levels of EE and NGMN reach very low or non-measurable levels within 3 days.

Table 5: Mean (%CV*) PK Parameters of NGMN and EE Following 3 Consecutive Cycles of ZAFEMY Wear on the Buttock
Analyte | Parameter | Cycle 1 Week 1 | Cycle 3 Week 1 | Cycle 3 Week 2 | Cycle 3 Week 3
NGMN | Css (ng/mL) AUC0-168 (ng·h/mL) t1/2 (h) | 0.70 (39.4) 107 (44.2) nc | 0.70 (41.8) 105 (43.2) nc | 0.80 (28.7) 132 (43.4) nc | 0.70 (45.3) 120 (43.9) 32.1 (40.3)
EE | Css (pg/mL) AUC0-168 (pg·h/mL) t1/2 (h) | 46.4 (38.5) 6,796 (39.3) nc | 47.6 (36.4) 7,160 (40.4) nc | 59.0 (42.5) 10,054 (41.8) nc | 49.6 (54.4) 8,840 (58.6) 21.0 (43.2)
nc = not calculated, *%CV is % of Coefficient of variation = 100 (standard deviation/mean)

Figure 3: Mean Serum NGMN Concentrations (ng/mL) in Healthy Female Volunteers Following Application of ZAFEMY on the Buttock for Three Consecutive Cycles (Vertical arrow indicates time of patch removal)

Figure 4: Mean Serum EE Concentrations (pg/mL) in Healthy Female Volunteers Following Application of ZAFEMY on the Buttock for Three Consecutive Cycles (Vertical arrow indicates time of patch removal.)

The absorption of NGMN and EE following application of ZAFEMY was studied under conditions encountered in a health club (sauna, whirlpool and treadmill) and in a cold water bath.

The results indicated that for NGMN, there were no significant treatment effects on Css or AUC when compared to normal wear. For EE, increased exposures were observed due to sauna, whirlpool and treadmill. There was no significant effect of cold water on these parameters.

Results from a study of consecutive ZAFEMY wear for 7 days and 10 days indicated that serum concentrations of NGMN and EE dropped slightly during the first 6 hours after the patch replacement, and recovered within 12 hours. By Day 10 of patch administration, both NGMN and EE concentrations had decreased by approximately 25% when compared to Day 7 concentrations.

Metabolism

Since norelgestromin and ethinyl estradiol are delivered transdermally, first-pass metabolism (via the gastrointestinal tract and/or liver) of NGMN and EE that would be expected with oral administration does not occur. Hepatic metabolism of NGMN occurs and metabolites include norgestrel, which is highly bound to SHBG, and various hydroxylated and conjugated metabolites. EE is also metabolized to various hydroxylated products and their glucuronide and sulfate conjugates.

Distribution

NGMN and norgestrel (a serum metabolite of NGMN) are highly bound (>97%) to serum proteins. NGMN is bound to albumin and not to SHBG, while norgestrel is bound primarily to SHBG, which limits its biological activity. EE is extensively bound to serum albumin and induces an increase in the serum concentrations of SHBG (see Table 5).

Elimination

Following removal of patches, the elimination kinetics of NGMN and EE were consistent for all studies with half-life values of approximately 28 hours and 17 hours, respectively. The metabolites of NGMN and EE are eliminated by renal and fecal pathways.

Transdermal versus Oral Contraceptives

The ZAFEMY transdermal patch delivers EE and NGMN over a seven-day period while oral contraceptives (containing NGM 250 mcg / EE 35 mcg) are administered on a daily basis. Figures 5 and 6 present mean PK profiles for EE and NGMN following administration of an oral contraceptive (containing NGM 250 mcg / EE 35 mcg) compared to the 7-day transdermal ZAFEMY patch (containing NGMN 3.15 mg / EE 0.289 mg) during Cycle 2 in 32 healthy female volunteers.

Figure 5: Mean Serum Concentration-Time Profiles of NGMN Following Once-Daily Administration of an Oral Contraceptive for 2 Cycles or Application of ZAFEMY for 2 Cycles to the Buttock in Healthy Female Volunteers. [Oral contraceptive: Cycle 2, Days 15 to 21, ZAFEMY: Cycle 2, Week 3]

Figure 6: Mean Serum Concentration-Time Profiles of EE Following Once-Daily Administration of an Oral Contraceptive for 2 Cycles or Application of ZAFEMY for 2 Cycles to the Buttock in Healthy Female Volunteers. [Oral contraceptive: Cycle 2, Days 15 to 21, ZAFEMY: Cycle 2, Week 3]

Table 6 provides the mean (%CV) for NGMN and EE pharmacokinetic (PK) parameters.

Table 6: Mean (%CV) NGMN and EE Steady-State Pharmacokinetic Parameters Following Application of ZAFEMY and Once-Daily Administration of an Oral Contraceptive (containing NGM 250 mcg / EE 35 mcg) in Healthy Female Volunteers
Parameter | ZAFEMY* | ORAL CONTRACEPTIVE†
NGMN‡
Cmax (ng/mL) | 1.12 (33.6) | 2.16 (25.2)
AUC0-168 (ng·h/mL) | 145 (36.8) | 123 (30.2)§
Css (ng/mL) | 0.888 (36.6) | 0.732 (30.2)¶
EE
Cmax (pg/mL) | 97.4 (31.6) | 133 (27.7)
AUC0-168 (pg·h/mL) | 12,971 (33.1) | 8,281 (26.9)§
Css (pg/mL) | 80.0 (33.5) | 49.3 (26.9)¶
* Cycle 2, Week 3
† Cycle 2, Day 21
‡ NGM is rapidly metabolized to NGMN following oral administration
§ Average weekly exposure, calculated as AUC24 × 7
¶ Cavg

In general, overall exposure for NGMN and EE (AUC and Css) was higher in subjects treated with ZAFEMY for both Cycle 1 and Cycle 2, compared to that for the oral contraceptive, while Cmax values were higher in subjects administered the oral contraceptive. Under steady-state conditions, AUC0-168 and Css for EE were approximately 55% and 60% higher, respectively, for the transdermal patch, and the Cmax was about 35% higher for the oral contraceptive, respectively. Inter-subject variability (%CV) for the PK parameters following delivery from ZAFEMY was higher relative to the variability determined from the oral contraceptive. The mean PK profiles are different between the two products and caution should be exercised when making a direct comparison of these PK parameters.

In Table 7, percent change in concentrations (%CV) of markers of systemic estrogenic activity (Sex Hormone Binding Globulin [SHBG] and Corticosteroid Binding Globulin [CBG]) from Cycle 1 Day 1 to Cycle 1 Day 22 is presented. Percent change in SHBG concentrations was higher for ZAFEMY users compared to women taking the oral contraceptive; percent change in CBG concentrations was similar for ZAFEMY and oral contraceptive users. Within each group, the absolute values for SHBG were similar for Cycle 1, Day 22 and Cycle 2, Day 22.

Table 7: Mean Percent Change (%CV) in SHBG and CBG Concentrations Following Once-Daily Administration of an Oral Contraceptive (containing NGM 250 mcg / EE 35 mcg) for One Cycle and Application of ZAFEMY for One Cycle in Healthy Female Volunteers
Parameter | ZAFEMY (% change from Day 1 to Day 22) | ORAL CONTRACEPTIVE (% change from Day 1 to Day 22)
SHBG | 334 (39.3) | 200 (43.2)
CBG | 153 (40.2) | 157 (33.4)

Drug Interactions

In a PK drug interaction study, oral administration of tetracycline HCl, 500 mg four times daily for 3 days prior to and 7 days during wear of ZAFEMY did not significantly affect the PK of NGMN or EE.

Use in Specific Populations

Effects of Age, Body Weight, Body Surface Area and Race

The effects of age, body weight, body surface area and race on the PK of NGMN and EE were evaluated in 230 healthy women from nine pharmacokinetic studies of single 7-day applications of ZAFEMY. For both NGMN and EE, increasing age, body weight and body surface area each were associated with slight decreases in Css and AUC values. However, only a small fraction (10% to 25%) of the overall variability in the PK of NGMN and EE following application of ZAFEMY may be associated with any or all of the above demographic parameters. There was no significant effect of race with respect to Caucasians, Hispanics and Blacks.

13 NONCLINICAL TOXICOLOGY

13.1 Carcinogenesis, Mutagenesis, and Impairment of Fertility

See Warnings and Precautions (5.3,5.12) and Use in Specific Populations (8.1).

Norelgestromin was tested in in vitro mutagenicity assays (bacterial plate incorporation mutation assay, CHO/HGPRT mutation assay, chromosomal aberration assay using cultured human peripheral lymphocytes) and in one in vivo test (rat micronucleus assay) and found to have no genotoxic potential.

14 CLINICAL STUDIES

In 3 large clinical trials lasting 12 months, in North America, Europe and South Africa, 3,330 women (ages 18 to 45) completed 22,155 cycles of ZAFEMY patch use, the pregnancy rate in women aged 18 to 35 years was 1.07 (95% confidence interval 0.60, 1.76) per 100 woman-years of ZAFEMY patch use. The racial distribution was 91% Caucasian, 4.9% Black, 1.6% Asian, and 2.4% Other.

With respect to weight, 5 of the 15 pregnancies reported with ZAFEMY patch use were among women with a baseline body weight ≥ 198 lbs., which constituted < 3% of the study population. The greater proportion of pregnancies among women at or above 198 lbs. was statistically significant and suggests that ZAFEMY patch may be less effective in these women.

Patch Adhesion

In the clinical trials with ZAFEMY patch, approximately 2% of the cumulative number of patches completely detached and 3% partially detached. The proportion of subjects with at least 1 patch that completely detached ranged from 2% to 6%, with a reduction from Cycle 1 (6%) to Cycle 13 (2%). For instructions on how to manage detachment of patches, refer to Dosage and Administration (2).

16 HOW SUPPLIED/STORAGE AND HANDLING

16.1 How Supplied

ZAFEMY (norelgestromin and ethinyl estradiol transdermal system) is available in one strength of 150 mcg/day NGMN, USP and 35 mcg/day EE, USP.

ZAFEMY is a 12.5 cm^2 system with rounded corners with tan backing printed with “Norelgestromin and Ethinyl Estradiol 150/35 mcg per day” in brown ink, protected with a removable translucent oversized dimple slit-release liner. Each patch contains 3.15 mg of norelgestromin, USP and 0.289 mg of ethinyl estradiol, USP.

Each transdermal system is packaged in a protective pouch.

ZAFEMY is available in folding cartons of 1 cycle each (NDC 42291-930-03); each cycle contains 3 systems.

16.2 Special Precautions for Storage and Disposal

Store at 20° to 25°C (68° to 77°F); excursions permitted between 15° to 30°C (59° to 86°F) [see USP Controlled Room Temperature].

Store patches in their protective pouches. Apply immediately upon removal from the protective pouch.

Do not store in the refrigerator or freezer.

Used patches still contain some active hormones. The sticky sides of the patch should be folded together and the folded patch placed in a sturdy container, preferably with a child-resistant cap, and the container thrown in the trash. Used patches should not be flushed down the toilet.

For more information, go to www.avkare.com or call 1-855-361-3993

17 PATIENT COUNSELING INFORMATION

See FDA-approved patient labeling (Patient Information and Instructions for Use)

17.1 General

Counsel patients about the following information:

- Cigarette smoking increases the risk of serious cardiovascular events from combined hormonal contraceptive use, and that women who are over 35 years old and smoke should not use combined hormonal contraceptives.
- The use of CHCs increases the risk of VTE. However, pregnancy increases the risk of VTE as much or more than the use of CHCs. The risk of VTE in women using CHCs is 3 to 12 cases per 10,000 woman-years. The risk of VTE is highest during the first year of use of CHCs and when restarting hormonal contraception after a break of 4 weeks or longer. The risk of thromboembolic disease due to CHCs gradually disappears after use is discontinued.
- ZAFEMY does not protect against HIV infection (AIDS) and other sexually transmitted infections.
- The Warnings and Precautions associated with combined hormonal contraceptives.
- ZAFEMY is not to be used during pregnancy; if pregnancy occurs during use of ZAFEMY, instruct the patient to stop further use.
- Apply a single patch the same day every week (Weeks 1 through 3). Instruct patients what to do in the event a patch is missed. See “WHAT IF I FORGET TO CHANGE MY PATCH?” section in FDA-Approved Patient Labeling.
- Use a back-up or alternative method of contraception when enzyme inducers are used with ZAFEMY.
- Combined hormonal contraceptives may reduce breast milk production; this is less likely to occur if breastfeeding is well established.
- Women who start combined hormonal contraceptives postpartum, and who have not yet had a period, should use an additional method of contraception until they have used a patch for 7 consecutive days.
- Amenorrhea may occur. Consider pregnancy in the event of amenorrhea. Rule out pregnancy in the event of amenorrhea in two or more consecutive cycles, amenorrhea in one cycle if the woman has not adhered to the dosing schedule, or if associated with symptoms of pregnancy, such as morning sickness or unusual breast tenderness.
- If the ZAFEMY patch becomes partially or completely detached and remains detached, insufficient drug delivery occurs.

- A patch should not be re-applied if it is no longer sticky, becomes stuck to itself or another surface, has other material stuck to it, or has become loose or fallen off before. If a patch cannot be re-applied, a new patch should be applied immediately. Supplemental adhesives or wraps should not be used.
- A woman may not be protected from pregnancy if a patch is partially or completely detached for ≥24 hours (or if the woman is not sure how long the patch has been detached). She should start a new cycle immediately by applying a new patch. Back-up contraception, such as a condom and spermicide or diaphragm and spermicide, must be used for the first week of the new cycle.

All trademarks are the property of their respective owners.

Manufactured for:

AvKARE

Pulaski, TN 38478

Manufactured by:

Amneal Pharmaceuticals LLC

Piscataway, NJ 08854

Mfg. Rev. 04-2022-04 AV 04/23

Patient Information

ZAFEMY® (za feʹ my)
(norelgestromin and ethinyl estradiol transdermal system)

What is the most important information I should know about ZAFEMY?

Do not use ZAFEMY if you smoke cigarettes and are over 35 years old. Smoking increases your risk of serious cardiovascular side effects from hormonal birth control methods, including death from heart attack, blood clots or stroke. This risk increases with age and the number of cigarettes you smoke.

Do not use ZAFEMY if you have an increased risk for blood clots.

Do not use ZAFEMY if your Body Mass Index (BMI) is 30 kg/m^2 or more. Women with a BMI of 30 kg/m^2 or more who use ZAFEMY may be at a higher risk for developing blood clots compared to women with a BMI lower than 30 kg/m^2.

Hormonal birth control methods help to lower the chances of becoming pregnant. They do not protect against HIV infection (AIDS) and other sexually transmitted infections.

What is ZAFEMY?

ZAFEMY is a birth control patch for women with a BMI less than 30 kg/m^2. It contains two female hormones, an estrogen called ethinyl estradiol, and a progestin called norelgestromin.

Hormones from ZAFEMY get into the blood stream and are processed by the body differently than hormones from birth control pills. You will be exposed to about 60% more estrogen if you use ZAFEMY than if you use a typical birth control pill containing 35 micrograms of estrogen. In general, increased estrogen may increase the risk of side effects.

How well does ZAFEMY work?

Your chance of getting pregnant depends on how well you follow the directions for using ZAFEMY. The better you follow the directions, the less chance you have of getting pregnant.

In clinical studies, 1 to 2 out of 100 women got pregnant during the first year that they used ZAFEMY.

ZAFEMY may not be as effective in women weighing more than 198 lbs. (90 kg). If you weigh more than 198 lbs. (90 kg), talk to your healthcare provider about which method of birth control is right for you.

The following chart shows the chance of getting pregnant for women who use different methods of birth control. Each box on the chart contains a list of birth control methods that are similar in effectiveness. The most effective methods are at the top of the chart. The box on the bottom of the chart shows the chance of getting pregnant for women who do not use birth control and are trying to get pregnant.

Do not use ZAFEMY if you:

- smoke and are over 35 years old
- have or have had blood clots in your arms, legs, eyes or lungs
- have an inherited problem that makes your blood clot more than normal
- have had a stroke
- have had a heart attack
- have certain heart valve problems or heart rhythm problems that can cause blood clots to form in the heart
- have high blood pressure that medicine cannot control
- have diabetes with kidney, eye, nerve, or blood vessel damage
- have had certain kinds of severe migraine headaches with aura, numbness, weakness or changes in vision, or have any migraine headaches if you are over age 35
- have a BMI of 30 or more
- have liver disease, including liver tumors, take any Hepatitis C drug combination containing ombitasvir/paritaprevir/ritonavir, with or without dasabuvir. This may increase levels of the liver enzyme “alanine aminotransferase” (ALT) in the blood.
- have unexplained vaginal bleeding
- are pregnant or think you may be pregnant. However, ZAFEMY is not known to cause birth defects when used by accident during pregnancy.
- have had breast cancer or any cancer that is sensitive to female hormones

Hormonal birth control methods may not be a good choice for you if you have ever had jaundice (yellowing of the skin or eyes) caused by pregnancy or related to previous use of hormonal birth control.

Tell your healthcare provider if you have ever had any of the above conditions. Your healthcare provider may recommend another method of birth control.

Before you use ZAFEMY, tell your healthcare provider:

- about all your medical conditions
- if you are pregnant or think you are pregnant
- if you are scheduled for surgery. ZAFEMY may increase your risk of blood clots after surgery. You should stop using your ZAFEMY patch at least 4 weeks before you have surgery and not restart it until at least 2 weeks after your surgery.
- if you are scheduled for any laboratory tests. Certain blood tests may be affected by hormonal birth control methods.
- are breastfeeding or plan to breastfeed. Hormonal birth control methods that contain estrogen, like ZAFEMY, may decrease the amount of milk you make. A small amount of hormones from the ZAFEMY patch may pass into your breast milk. Consider another method of birth control until you are ready to stop breastfeeding.

Tell your healthcare provider about all medicines and herbal products that you take.

Some medicines and herbal products may make hormonal birth control less effective, including, but not limited to:

- certain seizure medicines (carbamazepine, felbamate, oxcarbazepine, phenytoin, rufinamide, and topiramate)
- aprepitant
- barbiturates
- bosentan
- griseofulvin
- certain combinations of HIV medicines (nelfinavir, ritonavir, ritonavir-boosted protease inhibitors)
- certain non-nucleoside reverse transcriptase inhibitors (nevirapine)
- rifampin and rifabutin
- St. John’s wort

Use another birth control method (such as a condom and spermicide or diaphragm and spermicide) when you take medicines that may make the ZAFEMY patch less effective.

Some medicines and grapefruit juice may increase your level of the hormone ethinyl estradiol if used together, including:

- acetaminophen
- ascorbic acid
- medicines that affect how your liver breaks down other medicines (itraconazole, ketoconazole, voriconazole, and fluconazole)
- certain HIV medicines (atazanavir, indinavir)
- atorvastatin
- rosuvastatin
- etravirine

Hormonal birth control methods may interact with lamotrigine, an anti-seizure medicine used for epilepsy. This may increase the risk of seizures, so your healthcare provider may need to adjust the dose of lamotrigine.

Women on thyroid replacement therapy may need increased doses of thyroid hormone.

Know the medicines you take. Keep a list of them to show your doctor and pharmacist when you get a new medicine.

How should I use ZAFEMY?

- For detailed instructions, see the step-by-step instructions for using ZAFEMY at the end of this Patient Information.
- Use ZAFEMY exactly as your healthcare provider tells you to use it.
- Wear 1 ZAFEMY patch at a time. Make sure you remove your old ZAFEMY patch before applying your new ZAFEMY patch.
- Do not skip using any ZAFEMY patches, even if you do not have sex often.
- ZAFEMY is applied in a 4-week cycle.

- Apply your ZAFEMY patch 1 time each week for 3 weeks (21 total days).
- Apply each new ZAFEMY patch on the same day of the week. This day will be your "Patch Change Day." For example, if you apply your first ZAFEMY patch on a Monday, all of your ZAFEMY patches should be applied on a Monday.
- Do not apply your ZAFEMY patch during Week 4. Make sure you remove your old ZAFEMY patch. This is your patch-free week. Your menstrual period should start during your patch-free week.
- Begin a new 4 week cycle by applying a new ZAFEMY patch on the day after Week 4 ends. Repeat the cycle of 3 weekly applications followed by a patch-free week.

- Your ZAFEMY patch should never be off for more than 7 days in a row. If your ZAFEMY patch is off for more than 7 days in a row and you have sex during this time, you could become pregnant.
- If you miss a period you might be pregnant. Some women miss their periods or have light periods on hormonal birth control methods even when they are not pregnant. Call your healthcare provider if you miss 1 period and have not used your ZAFEMY patch every day or you miss 2 periods in a row.

What are the possible side effects of ZAFEMY?

See "What is the most important information I should know about ZAFEMY?"

ZAFEMY may cause serious side effects, including:

- blood clots. Like pregnancy, hormonal birth control methods increase the risk of serious blood clots (see following graph), especially in women who have other risk factors, such as smoking, high blood pressure, high levels of fat in the blood, diabetes, obesity, a family history of blood clots, or age greater than 35. This increased risk is highest when you first start using hormonal birth control and when you restart the same or different hormonal birth control after not using it for a month or more. Some studies have reported that women who use ZAFEMY have a higher risk of getting a blood clot. Talk with your healthcare provider about your risk of getting a blood clot before using ZAFEMY or deciding which type of birth control is right for you.

It is possible to die or be permanently disabled from a problem caused by a blood clot, such as a heart attack or a stroke. Some examples of serious blood clots are blood clots in the:

- legs (deep vein thrombosis)
- lungs (pulmonary embolus)
- eyes (loss of eyesight)
- heart (heart attack)
- brain (stroke)

To put the risk of developing a blood clot into perspective: If 10,000 women who are not pregnant and do not use hormonal birth control are followed for one year, between 1 and 5 of these women will develop a blood clot. The figure below shows the likelihood of developing a serious blood clot for women who are not pregnant and do not use hormonal birth control, for women who use hormonal birth control, for pregnant women, and for women in the first 12 weeks after delivering a baby.

Likelihood of Developing a Serious Blood Clot (Venous Thromboembolism [VTE])

*CHC=combination hormonal contraception

**Pregnancy data based on actual duration of pregnancy in the reference studies. Based on a model assumption that pregnancy duration is nine months, the rate is 7 to 27 per 10,000 WY.

Call your healthcare provider right away if you have:

- leg pain that will not go away
- sudden shortness of breath
- sudden blindness, partial or complete
- severe pain or pressure in your chest
- sudden, severe headache unlike your usual headaches
- weakness or numbness in an arm or leg, or trouble speaking
- yellowing of the skin or eyeballs

Other serious risks include

- liver problems including liver tumors
- gallbladder disease
- high blood pressure

The most common side effects of ZAFEMY are:

- breast symptoms (discomfort, swelling, or pain)
- nausea
- headache
- skin irritation, redness, pain, swelling, itching or rash at the patch application site
- stomach pain
- pain during menstruation
- vaginal bleeding and menstrual disorders, such as spotting or bleeding between periods
- mood, affect and anxiety disorders

Some women have spotting or light bleeding, breast tenderness, or feel sick to their stomach during ZAFEMY use. If these symptoms occur, do not stop using the ZAFEMY patch. The problem will usually go away. If it doesn't go away, check with your healthcare provider.

Less common side effects are:

- acne
- less sexual desire
- bloating or fluid retention
- blotchy darkening of your skin, especially your face
- high blood sugar, especially in women with diabetes
- high fat (cholesterol, triglycerides) levels in the blood
- depression, especially if you have had depression in the past. Call your healthcare provider immediately if you have any thoughts of harming yourself.
- problems tolerating contact lenses
- weight gain

Tell your healthcare provider about any side effect that bothers you or that does not go away.

These are not all the possible side effects of ZAFEMY. For more information, ask your healthcare provider or pharmacist.

Call your healthcare provider for medical advice about side effects. You may report side effects to FDA at 1-800-FDA-1088.

How should I store and throw away used ZAFEMY patches?

- Store at room temperature between 59°F to 86°F (15°C to 30°C).
- Do not store ZAFEMY patches outside of their pouches. Apply immediately upon removal from the protective pouch.
- Do not store in the refrigerator or freezer.
- Used ZAFEMY patches still contain some active hormones. To throw away the ZAFEMY patch, fold the sticky side of the patch together, place it in a sturdy child-proof container, and place this container in the trash. Do not flush used ZAFEMY patches down the toilet.
- Return unused, unneeded, or expired patches to your pharmacist.

Keep ZAFEMY and all medicines out of the reach of children.

General information about the safe and effective use of ZAFEMY

Medicines are sometimes prescribed for purposes other than those listed in Patient Information. Do not use ZAFEMY for a condition for which it was not prescribed. Do not give ZAFEMY to other people, even if they have the same symptoms that you have. It may harm them.

You can ask your pharmacist or healthcare provider for information about ZAFEMY that is written for health professionals.

For more information, go to www.avkare.com or call 1-855-361-3993

What are the ingredients in ZAFEMY?

Active ingredient: norelgestromin, USP and ethinyl estradiol, USP

Inactive ingredient: pigmented polyethylene and polyester backing, polyisobutylene/polybutene adhesive, polybutene, crospovidone, oleyl alcohol, dipropylene glycol, polyethylene terephthalate (PET) film with a silicone coating.

Does hormonal birth control cause cancer?

It is not known if hormonal birth control causes breast cancer. Some studies, but not all, suggest that there could be a slight increase in the risk of breast cancer among current users with longer duration of use.

If you have breast cancer now, or have had it in the past, do not use hormonal birth control because some breast cancers are sensitive to hormones.

Women who use hormonal birth control methods may have a slightly higher chance of getting cervical cancer. However, this may be due to other reasons such as having more sexual partners.

What should I know about my period when using ZAFEMY?

When you use ZAFEMY you may have bleeding and spotting between periods, called unplanned bleeding. Unplanned bleeding may vary from slight staining between menstrual periods to breakthrough bleeding which is a flow much like a regular period. Unplanned bleeding occurs most often during the first few months of ZAFEMY use, but may also occur after you have been using the patch for some time. Such bleeding may be temporary and usually does not indicate any serious problems. It is important to continue using the patch on schedule. If the unplanned bleeding or spotting is heavy or lasts for more than a few days, you should discuss this with your healthcare provider.

What if I miss my scheduled period when using ZAFEMY?

Some women miss periods on hormonal birth control, even when they are not pregnant. However, if you go 2 or more months in a row without a period, or you miss your period after a month where you did not use all of your patches correctly, or you have symptoms associated with pregnancy, such as morning sickness or unusual breast tenderness, call your healthcare provider because you may be pregnant. Stop taking ZAFEMY if you are pregnant.

What if I want to become pregnant?

You may stop using ZAFEMY whenever you wish. Consider a visit with your healthcare provider for a pre-pregnancy checkup before you stop using the patch.

Zafemy is a registered trademark of Amneal Pharmaceuticals LLC.

Manufactured for:

AvKARE

Pulaski, TN 38478

Manufactured by:

Amneal Pharmaceuticals LLC

Piscataway, NJ 08854

Mfg. Rev. 04-2022-04 AV 04;23

INSTRUCTIONS FOR USE

ZAFEMY® (za feʹ my)

(norelgestromin and ethinyl estradiol transdermal system)

ZAFEMY is for skin use only.

Do not cut, damage, or alter the ZAFEMY patch in any way.

How to start using your ZAFEMY patch:

Figure A

- If you are not currently using hormonal birth control, you have 2 ways to begin using your ZAFEMY patch. Choose the way that is best for you:

- First day start: Apply your first ZAFEMY patch during the first 24 hours of your menstrual period.
- Sunday start: Apply your first ZAFEMY patch on the first Sunday after your menstrual period begins. Use a non-hormonal contraceptive method of birth control, such as a condom and spermicide or diaphragm and spermicide, for the first 7 days of your first cycle only. If your period starts on Sunday, apply your first ZAFEMY patch that day, and no back-up birth control is needed.

- If you are changing from oral hormone birth control pills, a vaginal contraceptive ring or another contraceptive transdermal patch to the ZAFEMY patch:

- Complete your current oral hormone birth control pill cycle, vaginal ring cycle or contraceptive transdermal patch cycle. Apply your first ZAFEMY patch on the day you would normally start your next oral birth control pill, patch or insert your next vaginal ring.
- If you do not get your period within 1 week after taking your last active pill, removing your last vaginal ring or contraceptive transdermal patch, check with your healthcare provider to make sure you are not pregnant. You may still go ahead and start ZAFEMY patch for contraception.
- If you apply your ZAFEMY patch more than 1 week after taking your last active oral hormone birth control pill, removing your last vaginal ring or contraceptive transdermal patch, use a non-hormonal contraceptive method, such as a condom and spermicide or diaphragm and spermicide, with the ZAFEMY patch for the first 7 days of patch use.

- If you are starting ZAFEMY after childbirth:

- If you are not breastfeeding, wait 4 weeks before using ZAFEMY and use a non-hormonal contraceptive method of birth control, such as a condom and spermicide or diaphragm and spermicide, for the first 7 days of your first cycle only. If you have had sex since your baby was born, wait for your first period, or see your healthcare provider to make sure you are not pregnant before starting ZAFEMY.

- If you are starting ZAFEMY after a miscarriage or abortion:

- You may start ZAFEMY immediately after a miscarriage or abortion that occurs in the first 12 weeks (first trimester) of pregnancy. You do not need to use another contraceptive method.
- If you do not start ZAFEMY within 5 days after a first trimester miscarriage or abortion, use a non-hormonal contraceptive method of birth control, such as a condom and spermicide or diaphragm and spermicide, while you wait for your period to start. You have 2 ways to begin using your ZAFEMY patch. Choose the way that is best for you:

- First day start: Apply your first ZAFEMY patch during the first 24 hours of your menstrual period.
- Sunday start: Apply your first ZAFEMY patch on the first Sunday after your menstrual period begins. Use a non-hormonal contraceptive method of birth control, such as a condom and spermicide or diaphragm and spermicide, for the first 7 days of your first cycle only. If your period starts on Sunday, apply your first ZAFEMY patch that day, and no back-up birth control is needed.

- If you are starting ZAFEMY after a miscarriage or abortion that occurs after the first 12 weeks of pregnancy (second trimester), wait 4 weeks before using ZAFEMY and use a non-hormonal contraceptive method of birth control, such as a condom and spermicide or diaphragm and spermicide, for the first 7 days of your first cycle only. If you have had sex since your miscarriage or abortion, wait for your first period, or see your healthcare provider to make sure you are not pregnant before starting ZAFEMY.

Figure B is a picture of the ZAFEMY patch.

Figure B

Step 1. Choose a place on your body for your ZAFEMY patch

- The ZAFEMY patch may be placed on your upper outer arm, abdomen, buttock or back in a place where it will not be rubbed by tight clothing. Avoid the waistline because clothing and belts may cause your patch to be rubbed off.
- Do not apply the patch to your breasts.
- Apply the ZAFEMY patch only to skin that is clean, dry, and free of any powder, make-up, cream, oil, or lotion.
- Do not apply the ZAFEMY patch to cut or irritated skin, or in the same location as the previous ZAFEMY patch.

Step 2: Apply your ZAFEMY patch

- Tear open the pouch at the top edge. Peel open the foil pouch that contains the ZAFEMY patch and its clear plastic cover. Gently remove the ZAFEMY patch and its plastic cover together from the pouch, being careful not to separate the patch from the clear plastic cover.

- Using a fingernail, peel away half of the clear plastic. Avoid touching the sticky surface with your fingers.

- Apply the sticky side of the ZAFEMY patch to clean, dry skin. Remove the other half of the clear plastic and apply the entire patch to your skin.

- Press firmly on the ZAFEMY patch with the palm of your hand for 10 seconds, making sure that the whole patch sticks to your skin.
- Run your fingers over the entire surface area to smooth out any “wrinkles” around the outer edges of the ZAFEMY patch.
- Check your ZAFEMY patch every day to make sure all edges are sticking correctly.

Step 3: Throwing away your ZAFEMY patch

- To throw away the ZAFEMY patch, fold the sticky side of the patch together, place it in a sturdy child-proof container, and place the container in the trash.
- Used ZAFEMY patches should not be flushed in the toilet.

Important notes:

- Your ZAFEMY patch must stick securely to your skin to work properly.
- Do not try to reapply a ZAFEMY patch if it is no longer sticky, if it has become stuck to itself or another surface, or if it has other material stuck to it. Do not tape or wrap the patch to your skin or reapply a patch that is partially adhered to clothing.

- If your ZAFEMY patch edge lifts up:

- Press down firmly on the patch with the palm of your hand for 10 seconds, making sure that the whole patch sticks to your skin. Run your fingers over the entire surface area to smooth out any “wrinkles” around the edges of the ZAFEMY patch.
- If your ZAFEMY patch does not stick completely, remove it and apply a replacement ZAFEMY patch.
- Do not tape or wrap the ZAFEMY patch to your skin or reapply a ZAFEMY patch that is partially stuck to clothing.

- If your ZAFEMY patch has been off or partially off:

- For less than 1 Day, try to reapply it. If the ZAFEMY patch does not stick completely, apply a new ZAFEMY patch immediately. No back-up contraception is needed and your "Patch Change Day" will stay the same.
- For more than 1 Day or if you are not sure for how long, you could become pregnant. To reduce this chance, apply a new ZAFEMY patch and start a new 4 week cycle. You will now have a new "Patch Change Day." Use a non-hormonal back-up contraception method such as a condom and spermicide or diaphragm and spermicide for the first week of your new 4 week ZAFEMY cycle.
- Talk to your healthcare provider about a replacement ZAFEMY patch prescription so you will always have an extra ZAFEMY patch available if needed.

- If you want to move your "Patch Change Day" to a different day of the week, finish your current cycle. Remove your third ZAFEMY patch on the correct day.

- During week 4, the "Patch Free Week" (Day 22 through Day 28), you may choose an earlier "Patch Change Day" by applying a new patch on the day you prefer. You now have a new Day 1 and a new "Patch Change Day."

- If your ZAFEMY patch becomes uncomfortable or your application site is red, painful or swollen, change your ZAFEMY patch. Remove your ZAFEMY patch and apply a new patch to a new location until your next "Patch Change Day."
- If you forget to change or remove your ZAFEMY patch:

- At the start of any patch cycle (Week 1, Day 1):

- You could become pregnant. You must use a back-up contraception method for 7 days. Apply the first ZAFEMY patch of your new cycle as soon as you remember. You now have a new "Patch Change Day" and a new Day 1.

- In the middle of your patch cycle (Week 2 or Week 3):

- If you forget to change your ZAFEMY patch for 1 or 2 days, apply a new ZAFEMY patch as soon as you remember. Apply your next patch on your normal "Patch Change Day." No back-up contraception method is needed.
- If you forget to change your ZAFEMY patch for more than 2 days, you could become pregnant. Start a new 4 week cycle as soon as you remember by putting on a new ZAFEMY patch. You now have a different "Patch Change Day" and a new Day 1. You must use a back-up contraception method for the first 7 days of your new cycle.

- At the end of your patch cycle (Week 4):

- If you forget to remove your ZAFEMY patch, take it off as soon as you remember. Start your next cycle on your normal "Patch Change Day," the day after Day 28. No back-up contraception method is needed.

- If you forget to apply your ZAFEMY patch at the start of your next patch cycle, you could become pregnant. Apply the first ZAFEMY patch of your new cycle as soon as you remember. You now have a new "Patch Change Day" and a new Day 1. Use a non-hormonal back-up contraception method such as a condom and spermicide or diaphragm and spermicide for the first 7 days of your new 4 week ZAFEMY cycle.
- If you have trouble remembering to change your ZAFEMY patch, talk to your healthcare provider about how to make patch changing easier or about using another method of contraception.
- If you are not sure how to use your ZAFEMY patch:

- Use a back-up contraception method such as a condom and spermicide or diaphragm and spermicide anytime you have sex. Make sure to have 1 of these non-hormonal contraception methods ready at all times.
- Talk to your healthcare provider for instructions on using your ZAFEMY patch.

This Patient Information and Instructions for Use have been approved by the U.S. Food and Drug Administration.

Zafemy is a registered trademark of Amneal Pharmaceuticals LLC

Manufactured for:
AvKARE

Pulaski, TN 38478

Manufactured by:

Amneal Pharmaceuticals LLC

Piscataway, NJ 08854

Mfg. Rev. 04-2022-04 AV 04/23